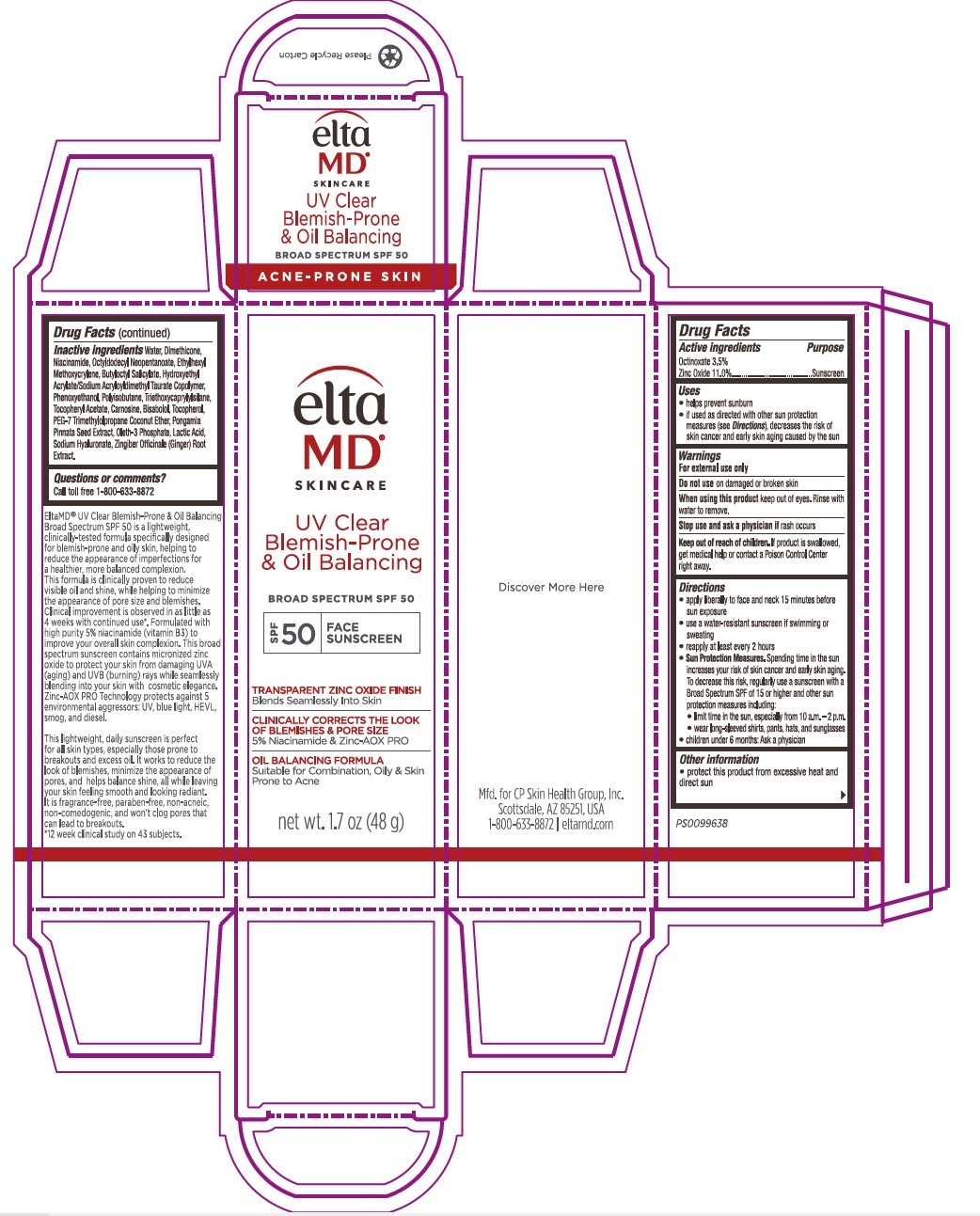 DRUG LABEL: EltaMD UV Clear Blemish-Prone and Oil Balancing
NDC: 72043-2518 | Form: CREAM
Manufacturer: CP Skin Health Group, Inc
Category: otc | Type: HUMAN OTC DRUG LABEL
Date: 20260127

ACTIVE INGREDIENTS: OCTINOXATE 35 g/100 g; ZINC OXIDE 110 g/100 g
INACTIVE INGREDIENTS: WATER; DIMETHICONE; NIACINAMIDE; OCTYLDODECYL NEOPENTANOATE; ETHYLHEXYL METHOXYCRYLENE; BUTYLOCTYL SALICYLATE; HYDROXYETHYL ACRYLATE/SODIUM ACRYLOYLDIMETHYL TAURATE COPOLYMER (45000 MPA.S AT 1%); PHENOXYETHANOL; POLYISOBUTYLENE (1000 MW); TRIETHOXYCAPRYLYLSILANE; .ALPHA.-TOCOPHEROL ACETATE; CARNOSINE; ETHYLHEXYLGLYCERIN; BISABOLOL; TOCOPHEROL; PEG-7 TRIMETHYLOLPROPANE COCONUT ETHER; PONGAMIA PINNATA SEED; OLETH-3 PHOSPHATE; LACTIC ACID; CANOLA OIL; BHT; SODIUM HYALURONATE; PHOSPHORIC ACID; ZINGIBER OFFICINALE (GINGER) ROOT OIL

EltaMD UV Clear Blemish-Prone and Oil Balancing

Warnings

For external use only. Do not use on damaged or broken skin. When using this product keep out of eyes. Rinse with water to remove. Stop use and ask a physician if rash occurs. If product is swallowed get medical help or contact a Poison Control Center right away.

Uses

Helps prevent sunburn. If used as directed with other sun protection measure (See Directions), decreases the risk of skin cancer and early skin aging caused by the sun.

Keep out of reach of children

Active Ingredients

Octinoxate 3.5%

Zinc Oxide 11.0%

Purpose

Sunscreen

Directions

Apply liberally 15 minutes before sun exposure. Use a water-resistant sunscreen if swimming or sweating. Reapply at least every 2 hours. Sun Protection Measures: Spending time in the sun increases your risk of skin cancer and early skin aging. To decrease this risk, regularly use a sunscreen with a broad-spectrum SPF of 15 or higher and other sun protection measures including: limit time in the sun, especially from 10 am to 2 pm. Wear long-sleeve shirts, pants, hats, and sunglasses. Children under 6 months: ask a physician.

Other Information

Protect this product from excessive heat and direct sun.

Inactive Ingredients

water, dimethicone, niacinamide, octyldodecyl neopentanoate, ethylhexyl methoxycrylene, butyloctyl salicylate, hydroxyethyl acrylate/sodium acryloldimethicone taurate copolymer, phenoxyethanol, polyisobutlene, triethoxycaprylylsilane, tocopheryl acetate, carnosine, bisabolol, tocpherol, peg-7 trimethylolpropane coconut ether, pongamia pinnata seed extract, oleth-3 phosphate, lactic acid, canola oil, BHT, sodium hyaluronate, phosphoric acid, zingiber officinale (Ginger) root extract

Questions or comments?

Call toll free 1-800-633-8872